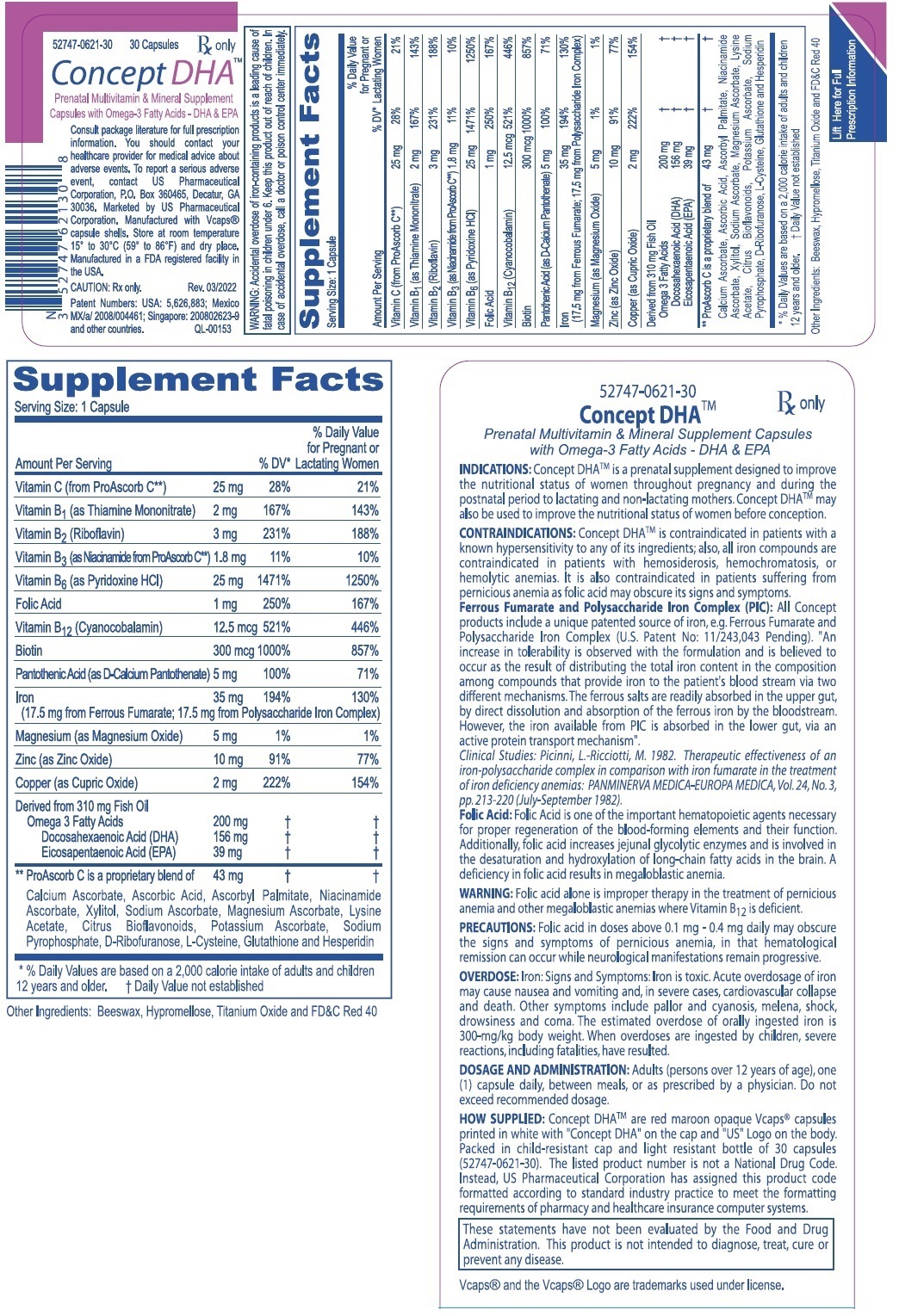 DRUG LABEL: Concept DHA
NDC: 52747-621 | Form: CAPSULE, LIQUID FILLED
Manufacturer: U.S. Pharmaceutical Corporation
Category: prescription | Type: HUMAN PRESCRIPTION DRUG LABEL
Date: 20221108

ACTIVE INGREDIENTS: FERROUS FUMARATE 17.5 mg/1 1; IRON  17.5 mg/1 1; ASCORBIC ACID 25 mg/1 1; FOLIC ACID 1 mg/1 1; THIAMINE MONONITRATE 2 mg/1 1; RIBOFLAVIN 3 mg/1 1; NIACIN 1.8 mg/1 1; CALCIUM PANTOTHENATE 5 mg/1 1; PYRIDOXINE HYDROCHLORIDE 25 mg/1 1; BIOTIN 300 ug/1 1; CYANOCOBALAMIN 12.5 ug/1 1; CUPRIC SULFATE 2 mg/1 1; MAGNESIUM SULFATE, UNSPECIFIED FORM 5 mg/1 1; ZINC SULFATE, UNSPECIFIED FORM 10 mg/1 1; OMEGA-3-ACID ETHYL ESTERS 200 mg/1 1
INACTIVE INGREDIENTS: YELLOW WAX; HYPROMELLOSE, UNSPECIFIED; TITANIUM DIOXIDE; FD&C RED NO. 40

see all prescribing information for Concept DHA

DESCRIPTION

DESCRIPTION: Each capsule contains: Ferrous Fumarate (Elemental Iron) . . . . . . . . . . 17.5 mg PolysaccharideIronComplex(ElementalIron).. 17.5mg
(Equivalent to about 35 mg of elemental iron) Vitamin C (from ProAscorb C‡) . . . . . . . . . . . . 25 mg FolicAcid.............................. 1mg ThiamineMononitrate(B1) ................ 2mg Riboflavin(B2) .......................... 3mg Niacin (B3, from ProAscorb C‡) . . . . . . . . . . . . 1.8 mg d-CalciumPantothenate(B5)................ 5mg PyridoxineHCI(B6) .................... 25mg Biotin (B7) . . . . . . . . . . . . . . . . . . . . . . . . . . . . 300 mcg Cyanocobalamin(B12) ................ 12.5mcg Copper(asCopperSulfate).................. 2mg
Magnesium(asMagnesiumSulfate) . . . . . . . . Zinc(asZincSulfate).................... Omega-3 Fatty Acids . . . . . . . . . ...........
(Derived from 310 mg Fish Oil) Docosahexaenoic Acid (DHA) . ........... Eicosapentaenoic Acid (EPA) . ........... . 5mg 10mg 200 mg156 mg 39 mg

CLINICAL STUDIES

Clinical Studies: Because Ferrous Fumarate is an organic complex, it contains no free ions, either ferric or ferrous. Polysaccharide Iron Complex is clinically non-toxic. Prior studies in rats demonstrated that Polysaccharide Iron Complex (PIC), administered as a single oral dose to Sprague Dawley rats did not produce evidence of toxicity at a dosage level of 5000 mg Iron/kg: (An Acute Oral Toxicity Study in Rats with Polysaccharide-Iron Complex. T.N.Merriman, M. Aikman and R.E. Rush, Springborn Laboratories, Inc. Spencerville, Ohio Study No. 3340.1 March - April 1994). Other clinical studies had demonstrated that Polysaccharide Iron gives a good hematopoietic response with an almost complete absence of the side effects usually associated with oral iron therapy. Picinni and Ricciotti suggested in 1982, that "the therapeutic effectiveness of Polysaccharide Iron Complex when compared with iron fumarate in the treatment of iron deficiency anemia, appears to be as active as the iron fumarate and as well tolerated, however, it exerted a greater influence on the level of hemoglobin and on the number of red cells..." and that, "it has been exceptionally well tolerated by all patients" (Picinni, L.-Ricciotti, M. 1982. Therapeutic effectiveness of an iron-polysaccharide complex in comparison with iron fumarate in the treatment of iron deficiency anemias): PANMINERVA MEDICA-EUROPA MEDICA, Vol. 24, No. 3, pp. 213-220 (July - September 1982). As mentioned above, the patented source of iron used in Concept DHATM (Ferrous Fumarate and Polysaccharide Iron Complex) provides a high level of elemental iron with a low incidence of gastric distress.
CONCLUSION: Based on the results of this study, the oral combination of Ferrous Fumarate and Polysaccharide Iron Complex was better tolerated and safer than the oral administration of Ferrous Fumarate alone. The conclusion of this research stated, that the addition of PIC to Ferrous Fumarate surprisingly allows the same concentration of Ferrous Fumarate to be better tolerated than the Ferrous Fumarate alone.

INDICATIONS AND USAGE

INDICATIONS: Concept DHATM is a prescription prenatal vitamin-mineral preparation containing omega-3 fatty acid supplements designed to supply nutritional supplementation for women throughout pregnancy and during the postnatal period to lactating and non-lactating mothers. Concept DHATM may also be used to improve the nutritional status of women before conception.

WARNINGS AND PRECAUTIONS

WARNING: Accidental overdose of iron-containing products is a leading cause of fatal poisoning in children under 6. Keep this product out of reach of children. In case of accidental overdose, call a doctor or poison control center immediately. WARNING: Ingestion of more than 3 grams of omega-3 fatty acids from fish oils per day may have potential antithrombotic effects, including an increased bleeding time and INR (international normalized ratio). DHA should be avoided in patients with inherited or acquired bleeding diatheses, including those taking anticoagulants.
WARNING: Folic acid alone is improper therapy in the treatment for pernicious anemia and other megaloblastic anemias where Vitamin B12 is deficient.
PRECAUTIONS: General: Folic acid in doses above 0.1 mg - 0.4 mg daily may obscure pernicious anemia, in that hematological remission can occur while neurological manifestations remain progressive.

DOSAGE AND ADMINISTRATION: Adults (persons over 12 years of age), one (1) capsule daily, between meals, or as prescribed by a physician. Do not exceed recommended dosage. Do not administer to children under the age of 12.

HOW SUPPLIED

HOW SUPPLIED: Concept DHATM are red maroon opaque Vcaps® capsules printed in white with "Concept DHA" on the cap "US" logo on the body. Packed in child-resistant cap and light resistant bottle of 30 capsules (52747-0621-30). The listed product number is not a National Drug Code. Instead, US Pharmaceutical Corporation has assigned this product code formatted according to standard industry practice to meet the formatting requirements of pharmacy and healthcare insurance computer systems.

These statements have not been evaluated by the Food and Drug Administration. This product is not intended to diagnose, treat, cure or prevent any disease.

Vcaps® and the Vcaps® Logo are trademarks used under license.